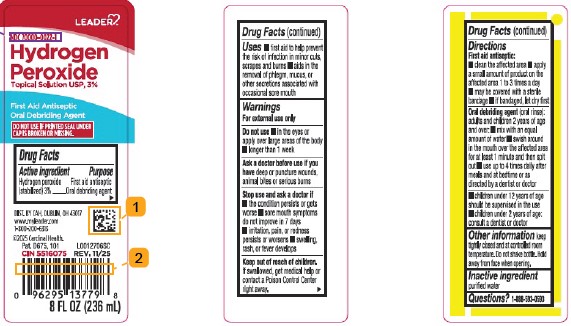 DRUG LABEL: Hydrogen Peroxide
NDC: 70000-0022 | Form: LIQUID
Manufacturer: Cardinal Health, 110 dba Leader
Category: otc | Type: HUMAN OTC DRUG LABEL
Date: 20260129

ACTIVE INGREDIENTS: HYDROGEN PEROXIDE 3 mL/100 mL
INACTIVE INGREDIENTS: WATER

Leader 871.001/871AA
Hydrogen Peroxide

Active Ingredient

Hydrogen peroxide (stabilized) 3%

Purpose

First aid antiseptic

Uses

- first aid to help prevent the risk of infection in minor cuts, scrapes and burns
- aids in the removal of phlegm, mucus, or other secretions associated with occasional sore mouth

Warnings

For external use only

Do not use

- in eyes or apply over large areas of the body
- longer than one week

Ask a doctor before use if you have

deep or puncture wounds, animal bites or serious burns

Stop use and ask a doctor if

- the condition persists or gets worse
- sore mouth symptoms do not improve in 7 days
- irritation, pain, or redness persists or worsens
- swelling, rash, or fever develops

Keep out of reach of children.

If swallowed, get medical help or contact a Poison Control Center right away.

Directions

First aid antiseptic:

- clean the affected area
- apply a small amount of product on the affected area 1 to 3 times a day
- may be covered with a sterile bandage
- if bandaged, let dry first

Oral debriding agent(oral rinse): adults and children 2 years of age and over:

- mix with an equal amount of water
- swish around in the mouth over the affected area for at least 1 minute and then spit out
- use up to 4 times daily after meals and at bedtime or as directed by a dentist or doctor

- children under 12 years of age should be supervised in the use of this product
- children under 2 years of age: consult a dentist or doctor

Other information

keep tightly closed and at controlled room temperature. Do not shake bottle. Hold sprayer tip away from face when opening.

Inactive ingredient

purified water

Questions?

1-888-593-0593

principal display panel

LEADER™

NDC 70000-0022-1

Hydrogen Peroxide

Topical Solution USP, 3%

First Aid Antiseptic

Oral Debriding Agent

DO NOT USE IF PRINTED SEAL UNDER CAP IS BROKEN OR MISSING.

DIST. BY CAH, DUBLIN, OH 43017

www.myleader.com

1-800-200-6313

©2025 Cardinal Health

Pat. D675, 101

CIN 5516075 REV. 11/25

8 FL OZ (236 mL)